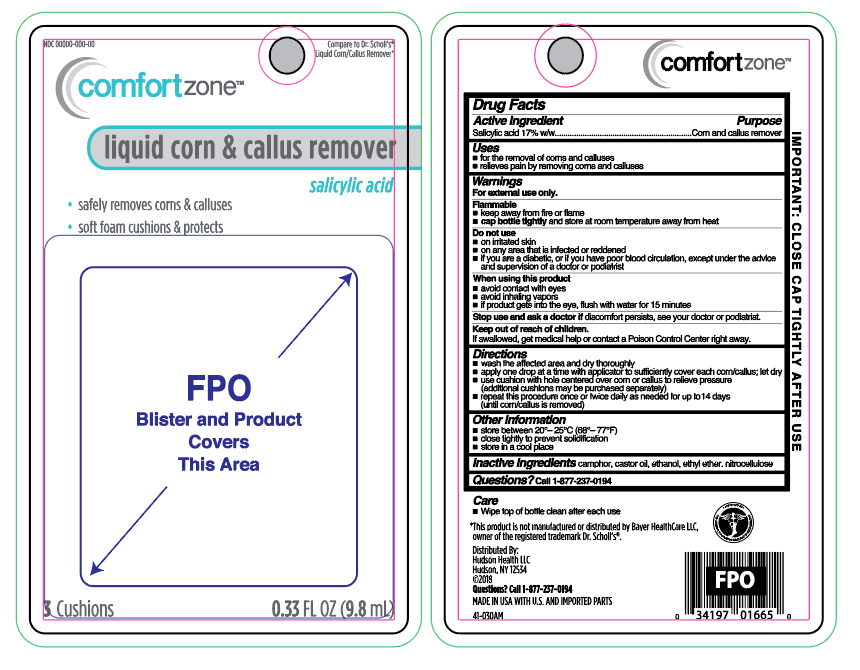 DRUG LABEL: Salicylic Acid
NDC: 72446-010 | Form: LIQUID
Manufacturer: Hudson Health LLC
Category: otc | Type: HUMAN OTC DRUG LABEL
Date: 20251008

ACTIVE INGREDIENTS: SALICYLIC ACID 0.17 mg/9.8 mL
INACTIVE INGREDIENTS: PYROXYLIN; CAMPHOR (NATURAL); CASTOR OIL

Comfortzone Liquid Corn & Callus Remover

Active ingredient

Salicylic acid 17%w/w

Purpose

Corn and callus remover

Uses

- for the removal of corns and calluses
- relieves pain by removing corns and calluses

Warnings

For external use only.

Flammable

- keep away from fire or flame
- cap bottle tightly and store at room temperature away heat

Do not use

- on irritated skin
- on any area that is infected or reddened
- if you are a diabetic, or if you have poor blood circulation, except under the advice and supervision of a doctor or podiatrist

When using this product

- avoid contact with eyes
- avoid inhaling vapors
- if product gets into the eyes, flush with water for 15 minutes

Stop and ask a doctor if

discomfort persists, see your doctor or podiatrist

Keep out of reach of children.

If swallowed, get medical help or contact a Poison Control Center right away.

Directions

- wash affected area and dry thoroughly
- apply one drop at a time with applicator, to sufficiently cover each corn/callus; let dry
- use cushions with hole centered over corn or callus to relieve pressure (additional cushions may be purchased separately)
- repeat this procedure once or twice daily as needed for up to 14 days (until corn/callus is removed)

Other information

store between 20°C to 30°C (68°F to 86°F)

Inactive ingredients

camphor, castro oil, ethanol, ethyl ether, nitrocellulose

Questions?

Call 1- 877-237-0194

Principal Display Panel

comfortzone

liquid corn & callus remover

salicylic acid

- safely removes corn & calluses
- soft foam cushions & protects

3 Cushions

0.33 FL OZ (9.8 mL)